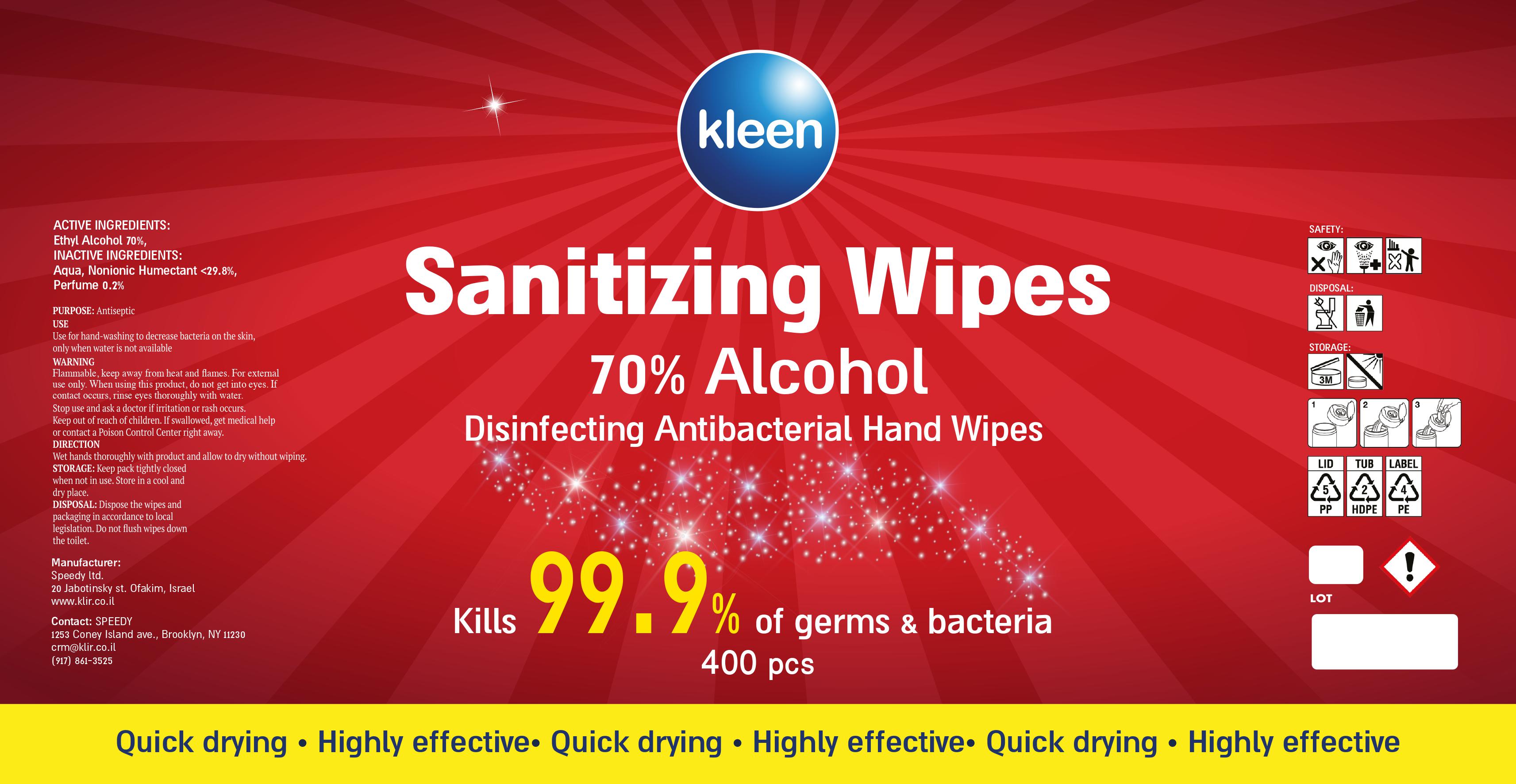 DRUG LABEL: Kleen Sanitizing Wipes
NDC: 81114-002 | Form: CLOTH
Manufacturer: Speedy Detergent Industries (2002) Ltd.
Category: otc | Type: HUMAN OTC DRUG LABEL
Date: 20201201

ACTIVE INGREDIENTS: ALCOHOL 70 g/100 g
INACTIVE INGREDIENTS: GLYCERIN; WATER

Kleen Sanitizing Wipes

Active Ingredient(s)

Alcohol 70%

Purpose

Antiseptic

Use

Use for hand-washing to decrease bacteria on the skin, only when water is not available.

Warnings

Flammable. Keep away from heat and flames. For external use only.

When using this product, do not get into eyes. In case of contact occurs, rinse eyes thoroughly with water.

Stop use and ask a doctor if irritation or rash occurs.

Keep out of reach of children. If swallowed, get medical help or contact a Poison Control Center right away.

Directions

Wet hands thoroughly with the product and allow to dry without wiping

Other information

Keep pack tightly closed when not in use. Store in a cool and dry place.

Inactive ingredients

Aqua, Nonionic Humectant <29.8%, Perfume 0.2%

DISPOSAL AND WASTE HANDLING

Dispose the wipes and packaging in accordance to local legislation. Do not flush wipes down the toilet.

Package Label - Principal Display Panel

kleen

Sanitizing Wipes

70% Alcohol

Disinfecting Antibacterial Hand Wipes

Kills 99.9% of germs and bacteria

Quick drying - Highly effective

Manufacturer:

Speedy ltd.

20 Jabotinsky st. Ofakim, Israel

www.klir.co.il

Contact: SPEEDY

1253 Coney Island ave. Brooklyn, NY 11230

crm@klir.co.il

(917) 861-3525